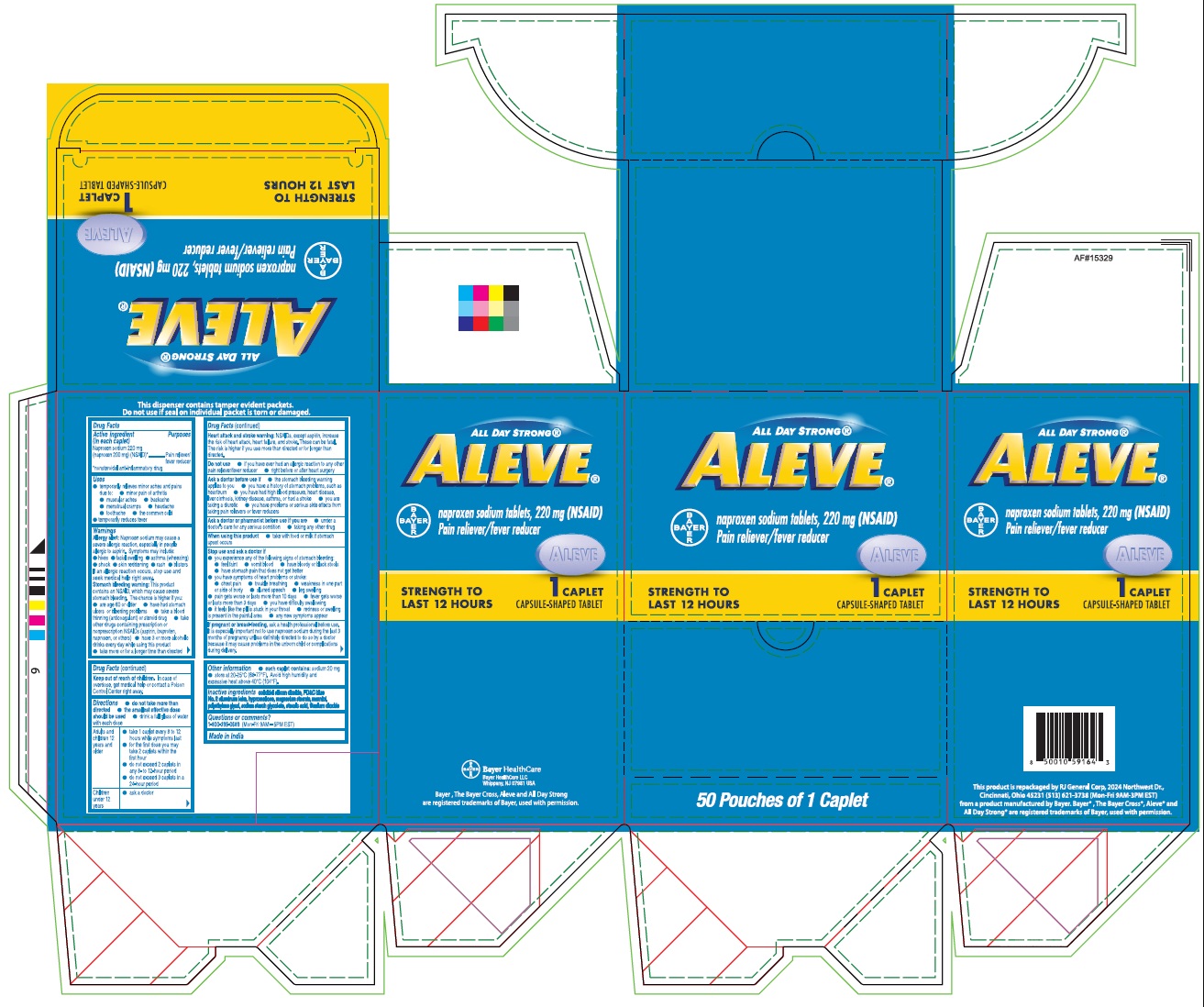 DRUG LABEL: Aleve
NDC: 70264-011 | Form: TABLET
Manufacturer: R J General Corporation
Category: otc | Type: HUMAN OTC DRUG LABEL
Date: 20251117

ACTIVE INGREDIENTS: NAPROXEN SODIUM 220 mg/1 1
INACTIVE INGREDIENTS: SILICON DIOXIDE; FD&C BLUE NO. 2 ALUMINUM LAKE; HYPROMELLOSE, UNSPECIFIED; MAGNESIUM STEARATE; POLYETHYLENE GLYCOL, UNSPECIFIED; SODIUM STARCH GLYCOLATE TYPE A; STEARIC ACID; TITANIUM DIOXIDE; MANNITOL

Aleve®

Drug Facts

Active ingredient (in each caplet)

Naproxen sodium 220 mg (naproxen 200 mg) (NSAID) [nonsteroidal anti-inflammatory drug]

Purposes

Pain reliever/fever reducer

Uses

- temporarily relieves minor aches and pains due to:
  - minor pain of arthritis
  - muscular aches
  - backache
  - menstrual cramps
  - headache
  - toothache
  - the common cold
- temporarily reduces fever

Warnings

Allergy alert

Naproxen sodium may cause a severe allergic reaction, especially in people allergic to aspirin. Symptoms may include:

- hives
- facial swelling
- asthma (wheezing)
- shock
- skin reddening
- rash
- blisters

If an allergic reaction occurs, stop use and seek medical help right away.

Stomach bleeding warning

This product contains an NSAID, which may cause severe stomach bleeding. The chance is higher if you:

- are age 60 or older
- have had stomach ulcers or bleeding problems
- take a blood thinning (anticoagulant) or steroid drug
- take other drugs containing prescription or nonprescription NSAIDs (aspirin, ibuprofen, naproxen, or others)
- have 3 or more alcoholic drinks every day while using this product
- take more or for a longer time than directed

Do not use

- if you have ever had an allergic reaction to any other pain reliever/fever reducer
- right before or after heart surgery

Ask a doctor before use if

- the stomach bleeding warning applies to you
- you have a history of stomach problems, such as heartburn
- you have high blood pressure, heart disease, liver cirrhosis, or kidney disease
- you are taking a diuretic
- you have problems or serious side effects from taking pain relievers or fever reducers
- you have asthma

Ask a doctor or pharmacist before use if you are

- under a doctor's care for any serious condition
- taking any other drug

When using this product

- take with food or milk if stomach upset occurs
- the risk of heart attack or stroke may increase if you use more than directed or for longer than directed

Stop use and ask a doctor if

- you experience any of the following signs of stomach bleeding:
  - feel faint
  - vomit blood
  - have bloody or black stools
  - have stomach pain that does not get better
- pain gets worse or lasts more than 10 days
- fever gets worse or lasts more than 3 days
- you have difficulty swallowing
- it feels like the pill is stuck in your throat
- redness or swelling is present in the painful area
- any new symptoms appear

PREGNANCY OR BREAST FEEDING

If pregnant or breast-feeding,ask a health professional before use. It is especially important not to use naproxen sodium during the last 3 months of pregnancy unless definitely directed to do so by a doctor because it may cause problems in the unborn child or complications during delivery.

Keep out of reach of children.In case of overdose, get medical help or contact a Poison Control Center right away.

Directions

- do not take more than directed
- the smallest effective dose should be used
- drink a full glass of water with each dose

Adults and children 12 years and older | - take 1 caplet every 8 to 12 hours while symptoms last - for the first dose you may take 2 caplets within the first hour - do not exceed 2 caplets in any 8- to 12-hour period - do not exceed 3 caplets in a 24-hour period
Children under 12 years | - ask a doctor

Other information

- each caplet contains:sodium 20 mg
- store at 20-25 ° C (68-77 ° F). Avoid high humidity and excessive heat above 40 ° C (104 ° F).

Inactive ingredients

colloidal silicon dioxide, FD&C blue No. 2 aluminum lake, hypromellose, magnesium stearate, mannitol, polyethylene glycol, soidum starch glycolate, stearic acid, titanium dioxide

Questions or comments?

1-800-395-0689(Mon - Fri 9AM - 5PM EST) or www.aleve.com

Made in India

PRINCIPAL DISPLAY PANEL - 50 Tablet Pouch Carton

ALL DAY STRONG®

ALEVE®

naproxen sodium tablets, 220 mg (NSAID)
Pain reliever/fever reducer

STRENGTH TO LAST 12 HOURS

1 CAPLET
CAPSULE-SHAPED TABLET